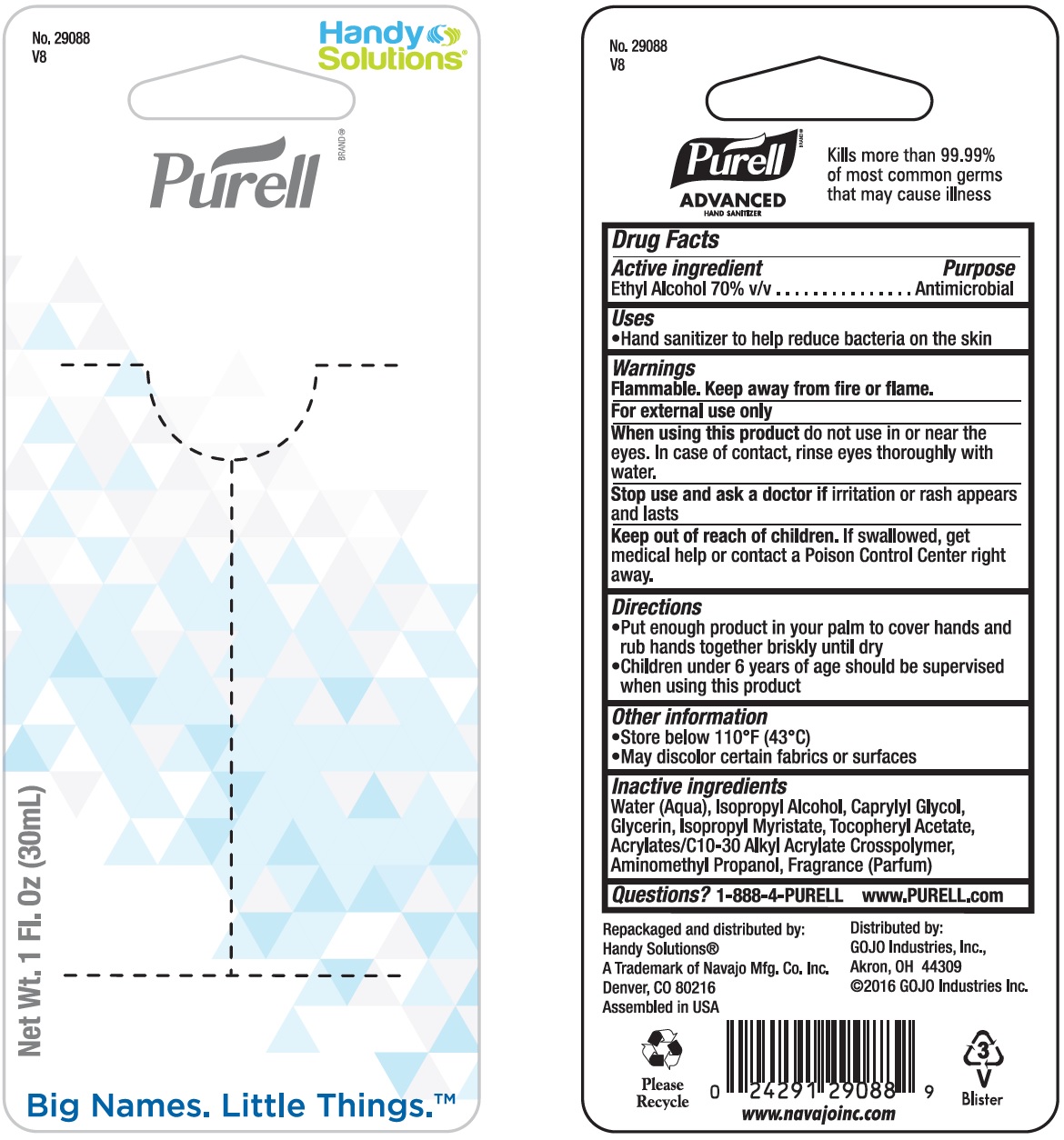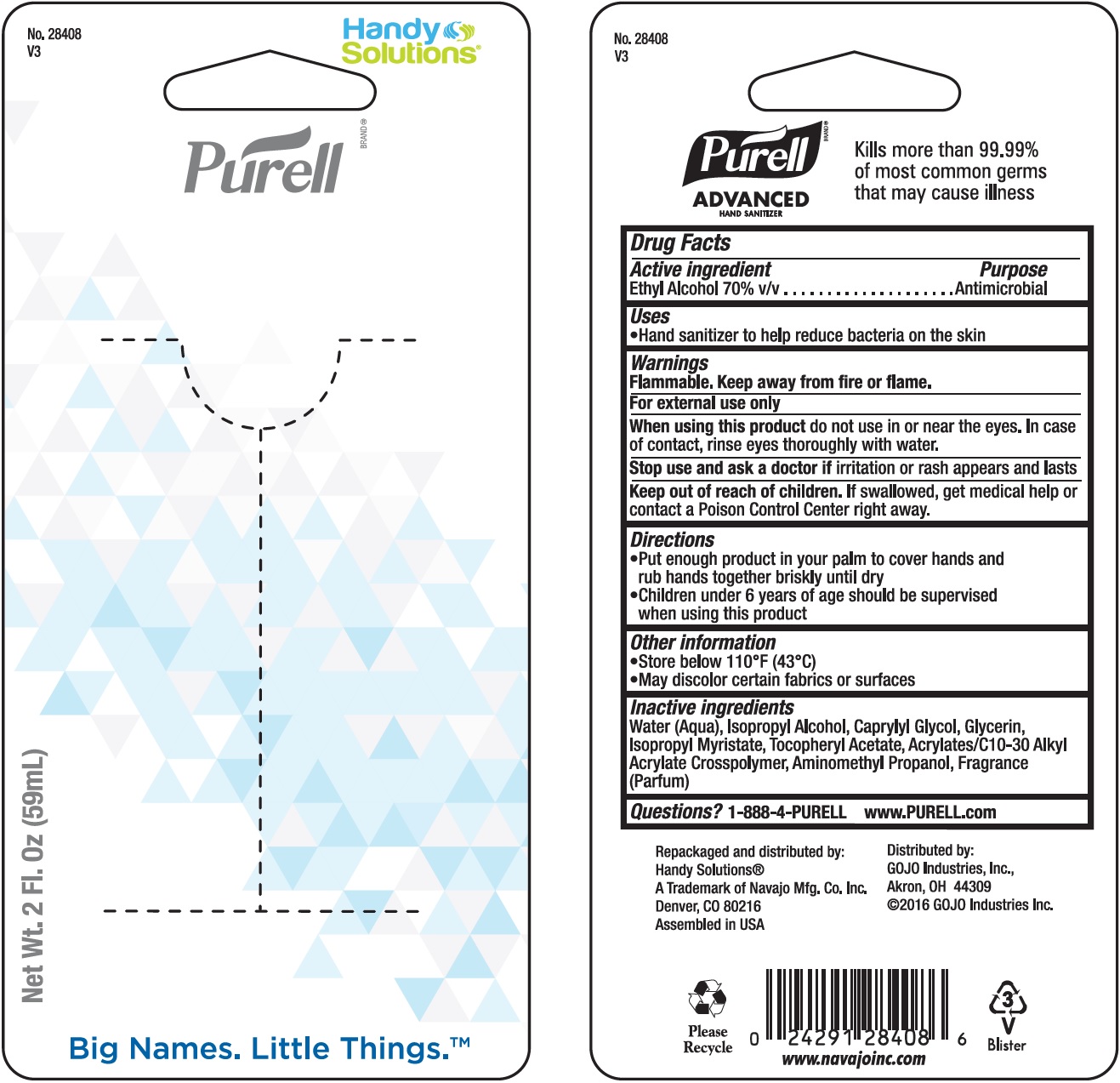 DRUG LABEL: Purell
NDC: 67751-188 | Form: GEL
Manufacturer: Navajo Manufacturing Company Inc.
Category: otc | Type: HUMAN OTC DRUG LABEL
Date: 20241002

ACTIVE INGREDIENTS: ALCOHOL 70 mL/100 mL
INACTIVE INGREDIENTS: WATER; ISOPROPYL ALCOHOL; CAPRYLYL GLYCOL; GLYCERIN; ISOPROPYL MYRISTATE; .ALPHA.-TOCOPHEROL ACETATE; AMINOMETHYLPROPANOL

Purell

Active ingredient

Ethyl Alcohol 70% v/v

Purpose

Antimicrobial

Uses

- Hand sanitized to help reduce bacteria on the skin

Warnings

Flammable. Keep away from fire or flame.

For external use only.

When using this product

do not use in or near the eyes. In case of contact, rinse eyes thoroughly with water.

Stop use and ask a doctor if

irritation or rash appears and lasts

Keep out of reach of children.

If swallowed, get medical help or contact a Poison Control Center right away.

Directions

- Put enough product in your palm to cover hands and rub hands together briskly until dry
- Children under 6 years of age should be supervised when using this product

Other information

- Store below 110°F (43°C)
- May discolor certain fabrics or surfaces

Inactive ingredients

Water (Aqua), Isopropyl Alcohol, Caprylyl Glycol, Glycerin, Isopropyl Myristate, Tocopheryl Acetate, Acrylates/C10-30, Alkly Acrylate, Crosspolymer, Aminomethyl Propanol, Fragrance (Parfum)

Questions?

1-888-4-PURELL www.PURELL.com